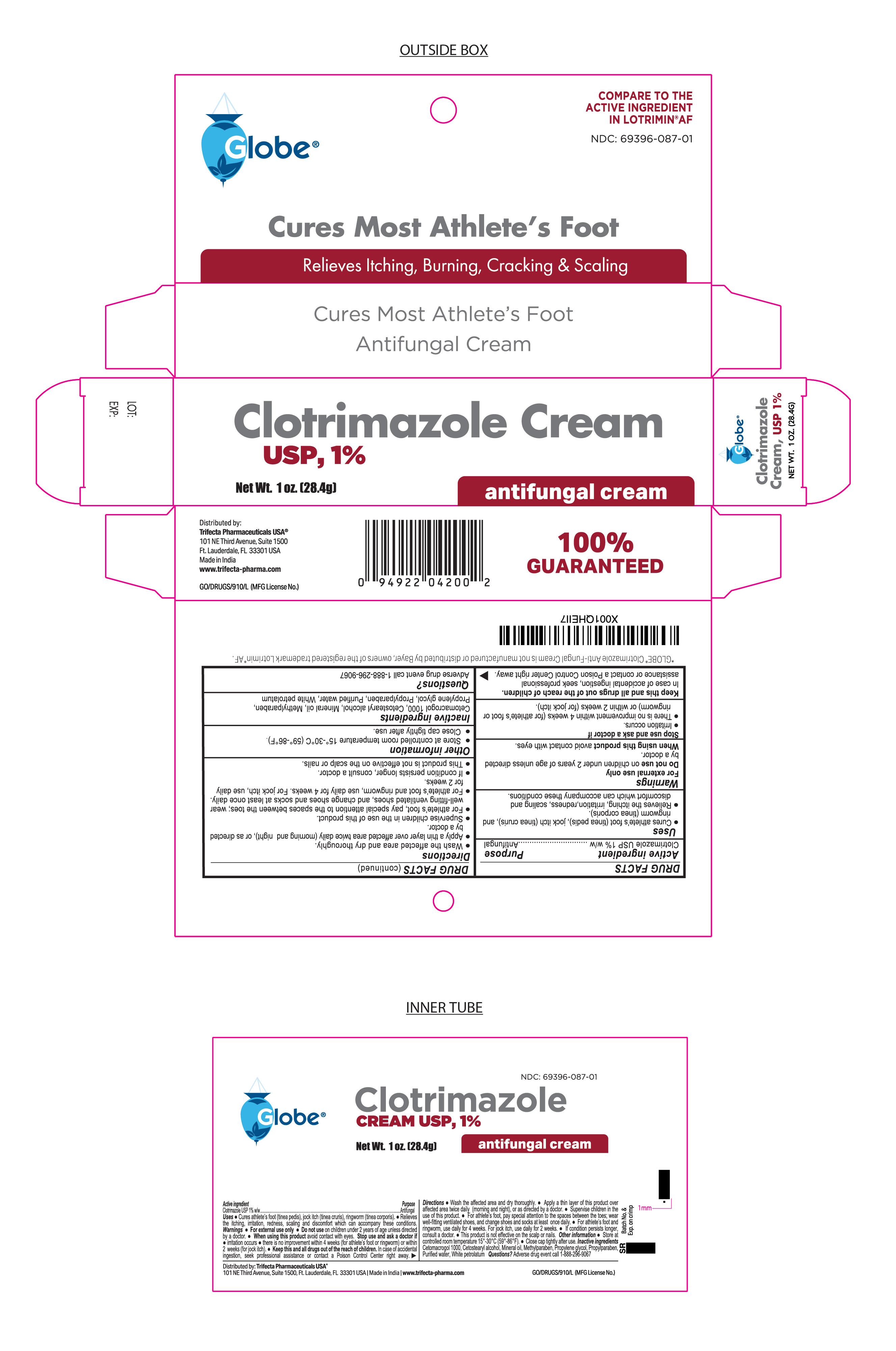 DRUG LABEL: Clotrimazole
NDC: 69396-087 | Form: CREAM
Manufacturer: TRIFECTA PHARMACEUTICALS USA LLC
Category: otc | Type: HUMAN OTC DRUG LABEL
Date: 20260301

ACTIVE INGREDIENTS: CLOTRIMAZOLE 1 g/100 g
INACTIVE INGREDIENTS: LIGHT MINERAL OIL; PETROLATUM; WATER; CETETH-20; PROPYLPARABEN; CETOSTEARYL ALCOHOL; METHYLPARABEN; PROPYLENE GLYCOL

Globe Clotrimazole cream USP, 1%

Active ingredient

Clotrimazole USP 1% w/w

Purpose

Antifungal Cream

KEEP OUT OF REACH OF CHILDREN

Keep this and all drugs out of the reach of children. In case of accidental ingestion, seek professional assistance or contact a Poison Control Center right away.

Uses

Cures athlete’s foot (tinea pedis), jock itch (tinea cruris), ringworm (tinea corporis). Relieves the itching, irritation, redness, scaling and discomfort which can accompany these conditions.

Warnings

● Do not use on children under 2 years of age unless directed by a doctor.

● For external use only

● Avoid contact with eyes.

Stop Use and ask a Doctor

Irritation occurs

There is no improvement within 4 weeks (for athlete's foot or ringworm) or within 2 weeks (for jock itch).

Directions

- Wash the affected area and dry thoroughly.

● Apply a thin layer of this product over affected area twice daily (morning and night), or as directed by a doctor.

● Supervise children in the use of this product.

● For athlete’s foot, pay special attention to the spaces between the toes; wear well-fitting ventilated shoes, and change shoes and socks at least once daily.

● For athlete’s foot and ringworm, use daily for 4 weeks. For jock itch, use daily for 2 weeks.

● If conditions persists longer, consult a doctor.

● This product is not effective on the scalp or nails.

Inactive Ingredients

Cetamacragol 1000, Cetostearyl alcohol, mineral oil, methylparaben, propylene glycol, propylparaben, purified water, white petrolatum.

Other Information

- store at controlled room temperature 15°-30°C (59°- 86°F)
- Close cap tightly after use.

Questions?

Adverse drug event call 1-888-296-9067
Dist. By Trifecta Pharmaceuticals USA™
101 NE Third Avenue, Suite 1500
Ft. Lauderdale, FL 33301, USA

Made in India

www.trifecta-pharma.com

Globe Clotrimazole Anti-Fungal Cream is not manufactured or distributed by Bayer, owners of the registered trademark Lotrimin AF.